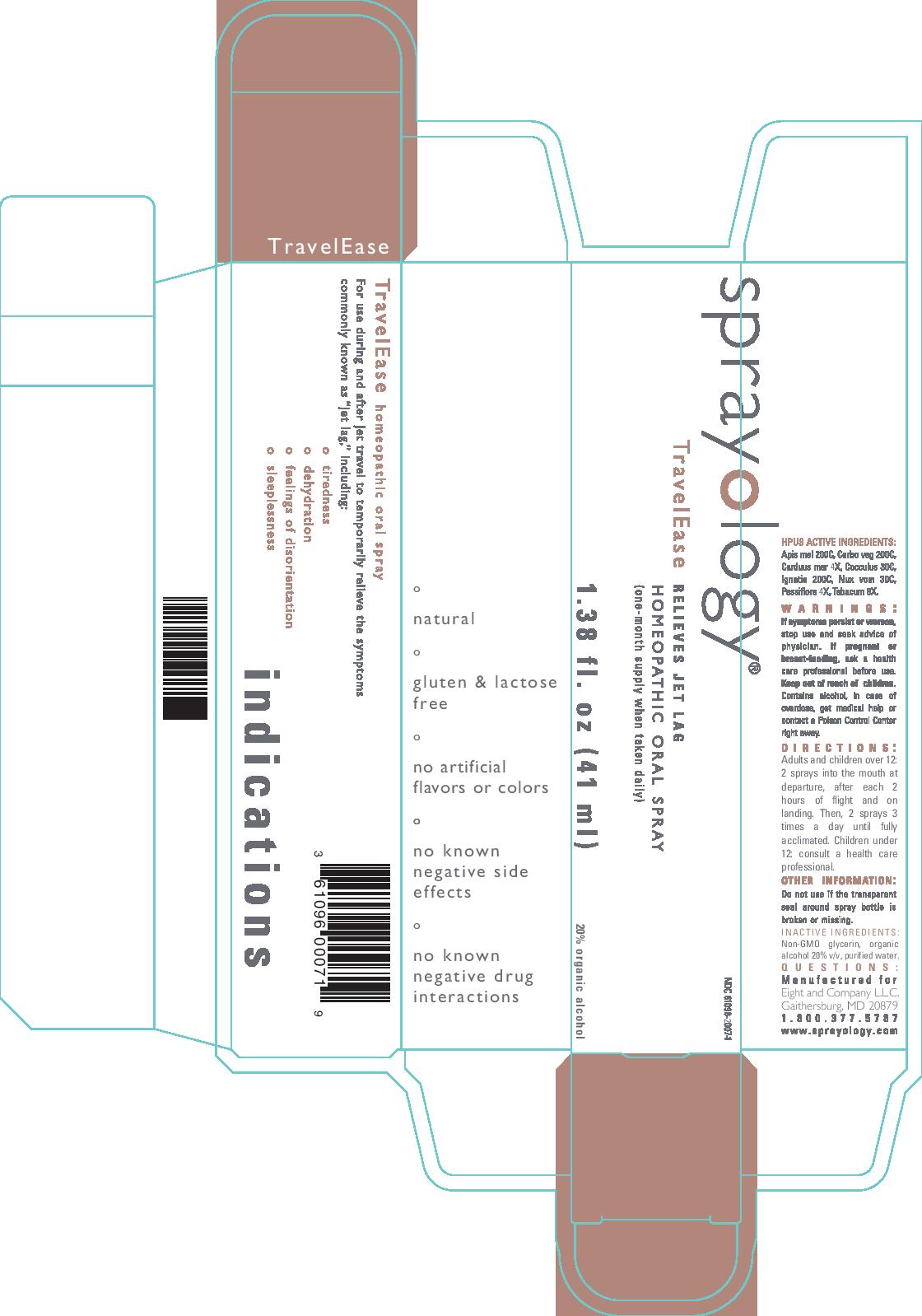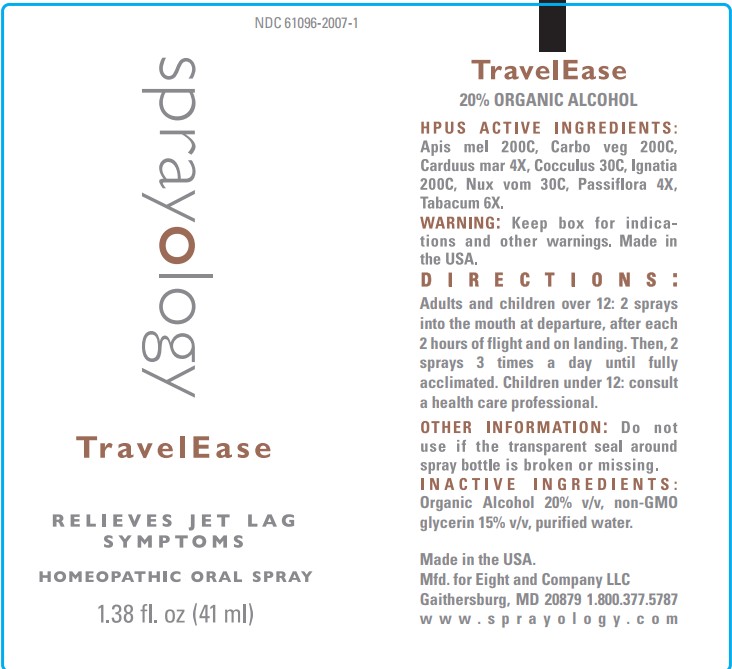 DRUG LABEL: Sprayology TravelEase
NDC: 61096-2007 | Form: LIQUID
Manufacturer: Eight and Company L.L.C
Category: homeopathic | Type: HUMAN OTC DRUG LABEL
Date: 20251224

ACTIVE INGREDIENTS: MILK THISTLE 4 [hp_X]/41 mL; ANAMIRTA COCCULUS SEED 30 [hp_C]/41 mL; STRYCHNOS IGNATII SEED 200 [hp_C]/41 mL; STRYCHNOS NUX-VOMICA SEED 30 [hp_C]/41 mL; PASSIFLORA INCARNATA FLOWERING TOP 4 [hp_X]/41 mL; TOBACCO LEAF 6 [hp_X]/41 mL; APIS MELLIFERA 200 [hp_C]/41 mL; ACTIVATED CHARCOAL 200 [hp_C]/41 mL
INACTIVE INGREDIENTS: GLYCERIN; ALCOHOL; WATER

TravelEase

ACTIVE INGREDIENT

Active Ingredients: Apis mel 200C, Carbo veg 200C, Carduus mar 4X, Cocculus 30C, Ignatia 200C, Nux vomica 30C, Passiflora 4X, Tabacum 6X.

WARNINGS

Warnings: If symptoms persist or worsen, stop use and seek advice of physician. If pregnant or breast-feeding, ask a health care professional before use. Keep out of reach of children. Contains alcohol, in case of overdose, get medical help or contact a Poison Control Center right away.

Keep out of reach of children.

PURPOSE

For use during and after jet travel to temporarily relieve the symptoms commonly known as "jet lag", including:

- tiredness
- dehydration
- feeling of disorientation
- sleeplessness

Directions:

- Adults and children over 12: 2 sprays into the mouth at departure, after each 2 hours of flight and on landing. Then 2 sprays 3 times a day until fully acclimated.
- Children Under 12: consult a health care professional.

Other Information: Do not use if the transparent seal around spray bottle is broken or missing.

INACTIVE INGREDIENT

Inactive Ingredients: Non-GMO Glycerin, organic alcohol 20% v/v, purified water.

INDICATIONS AND USAGE

For use during and after jet travel to temporarily relieve the symptoms commonly known as "jet lag", including:

° tiredness

° dehydration

° feeling of disorientation

° sleeplessness

-natural

-gluten & lactose free

-no artificial flavors or colors

-no known negative side effects

-no known negative drug interactions